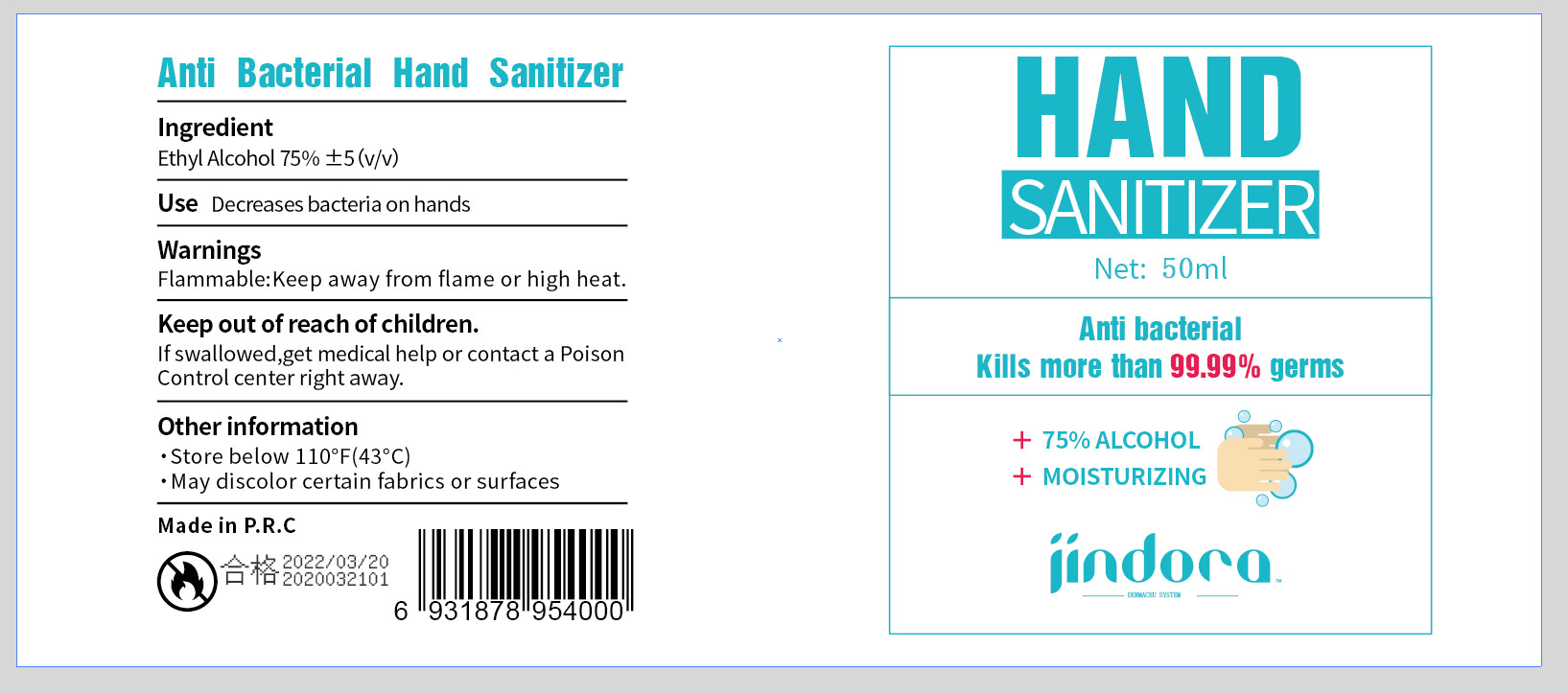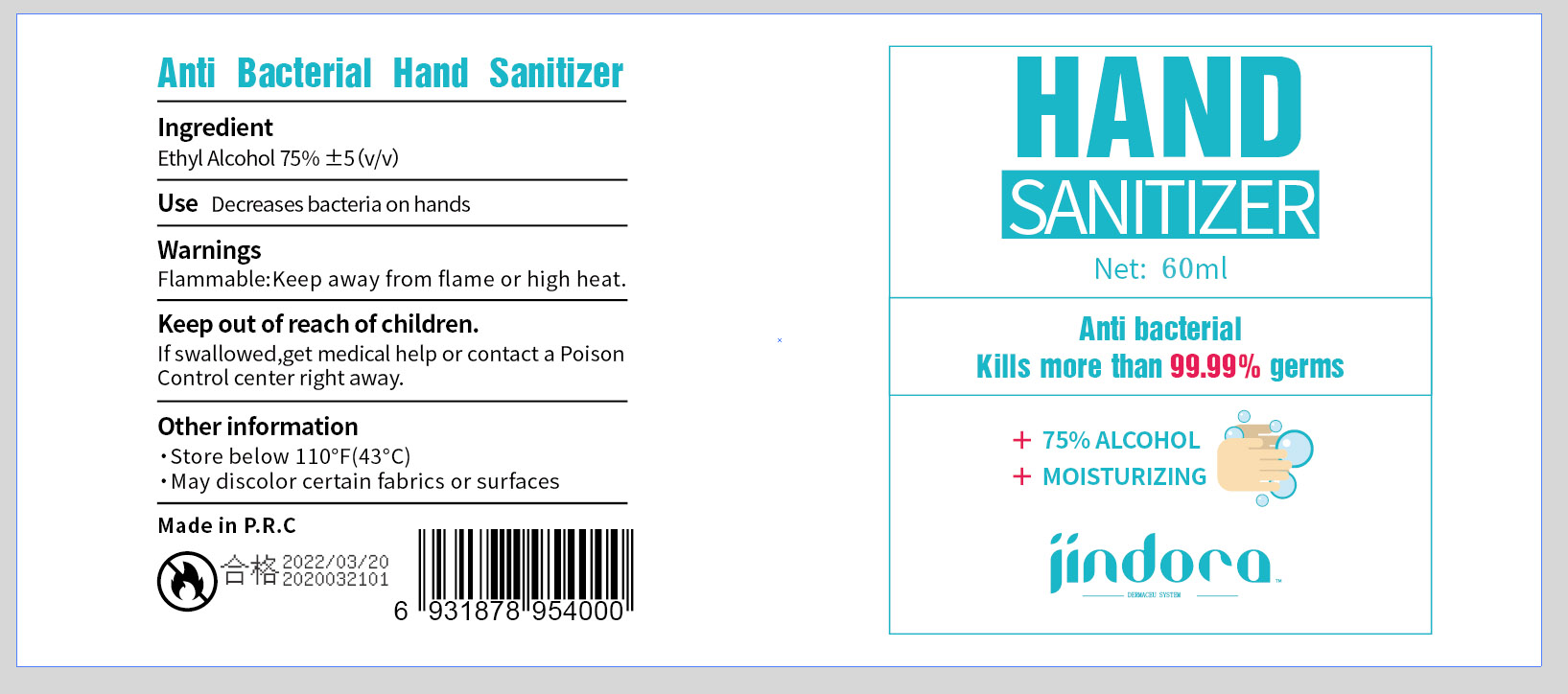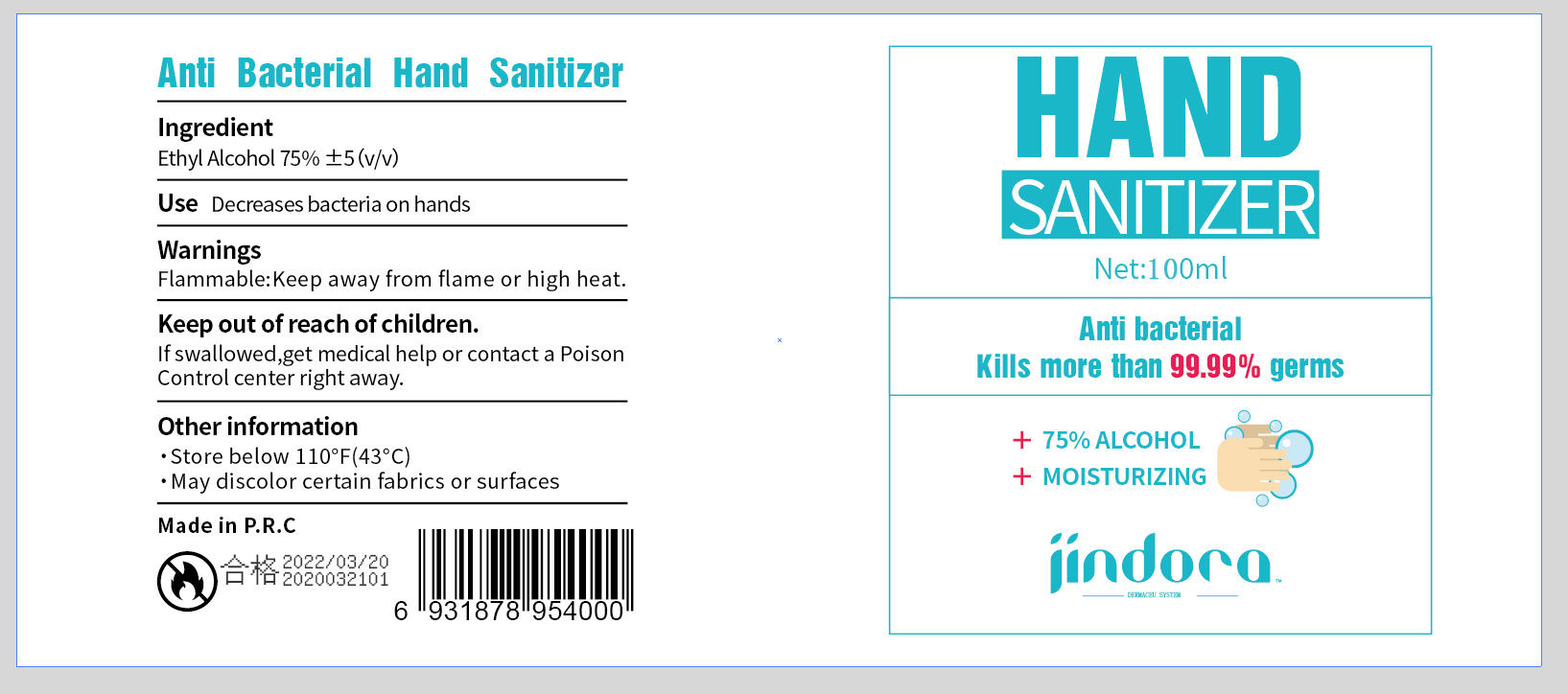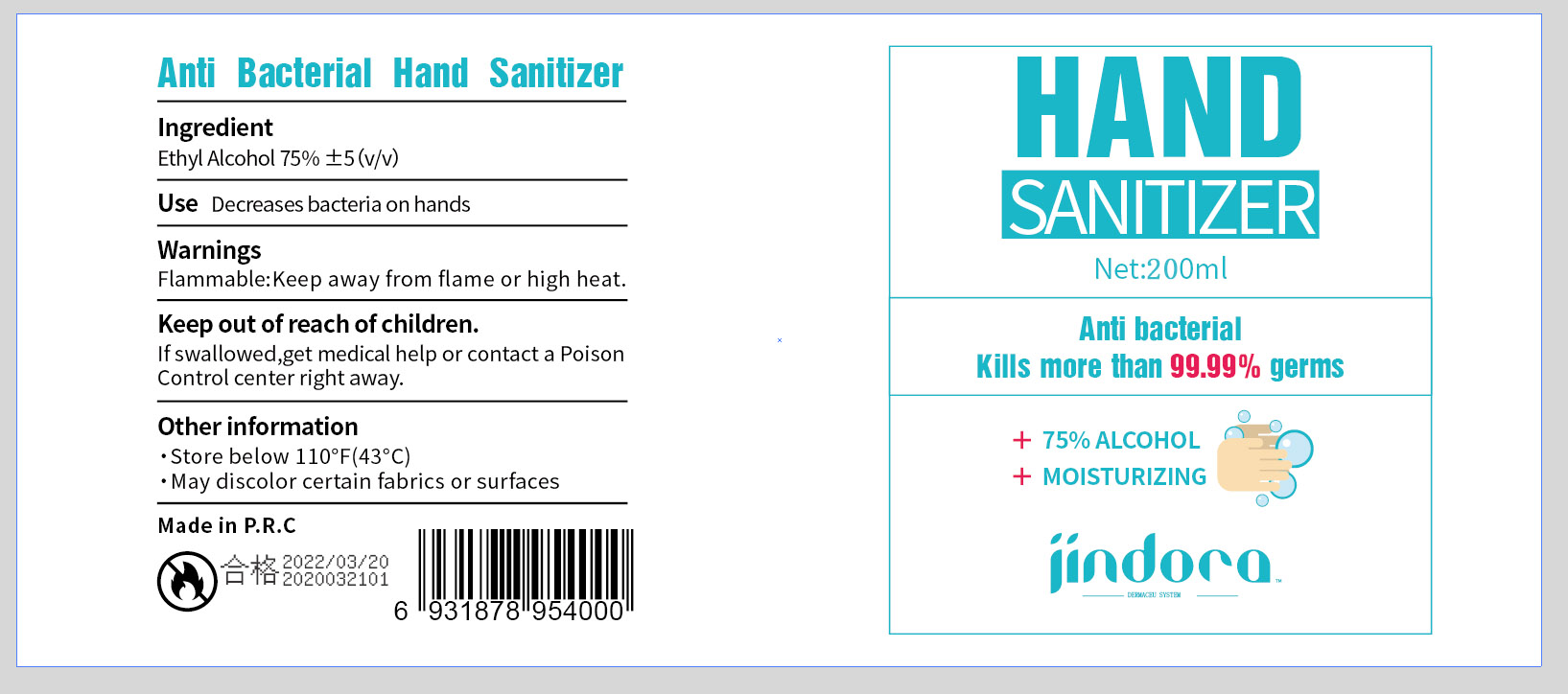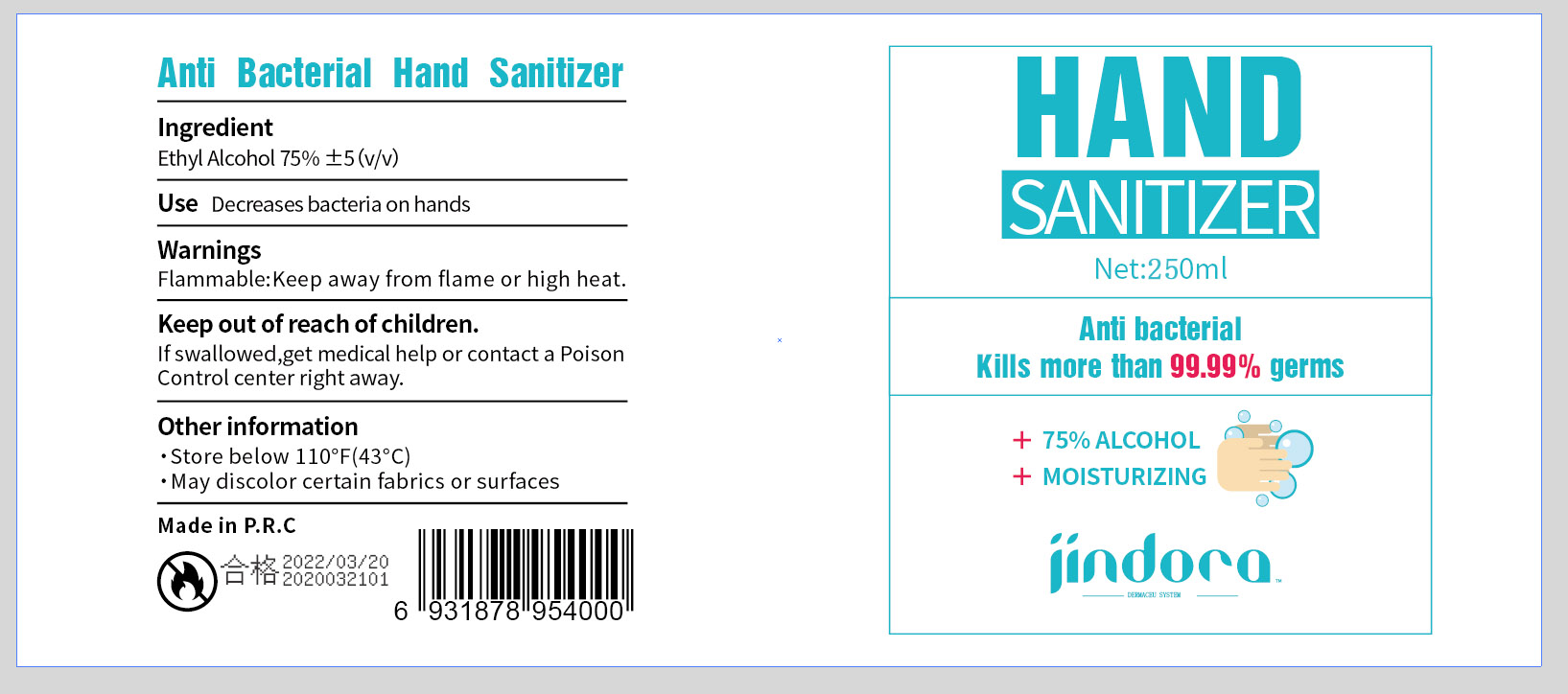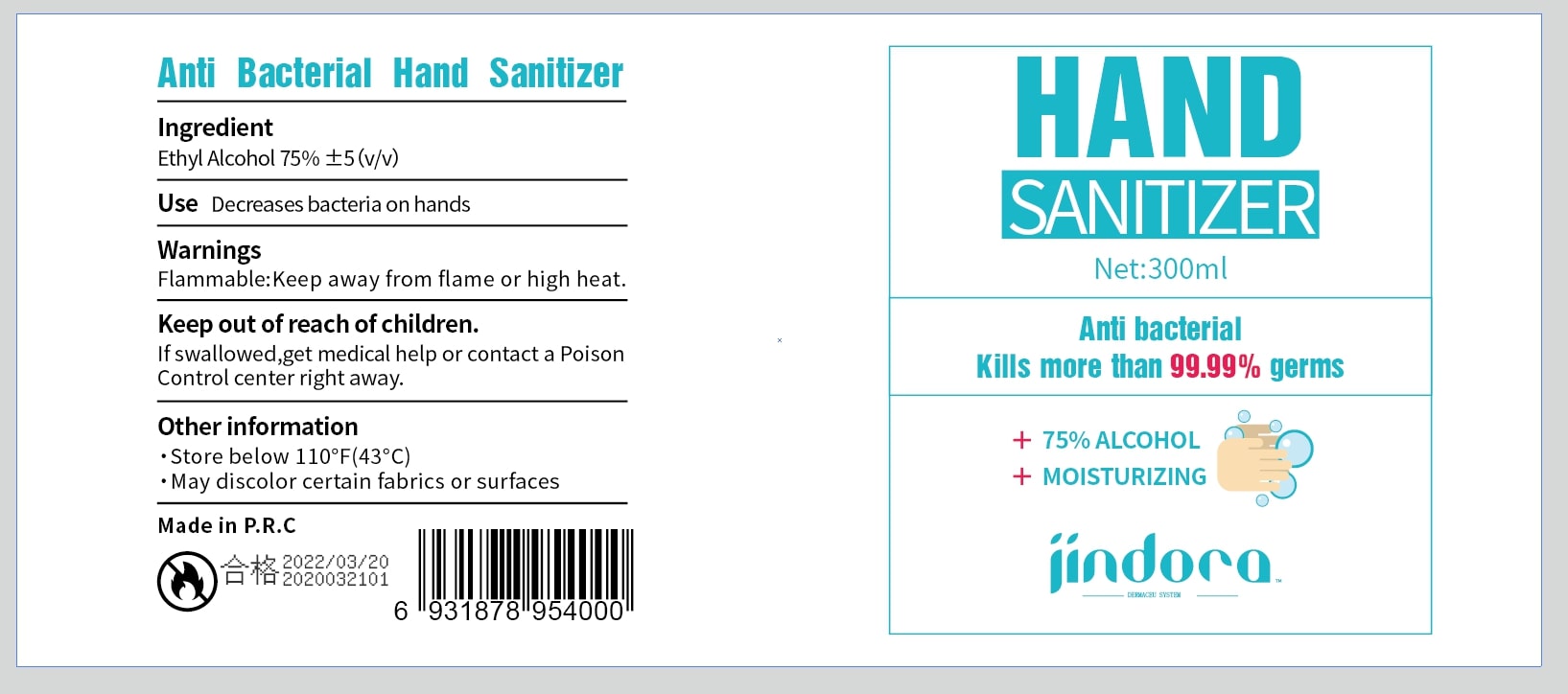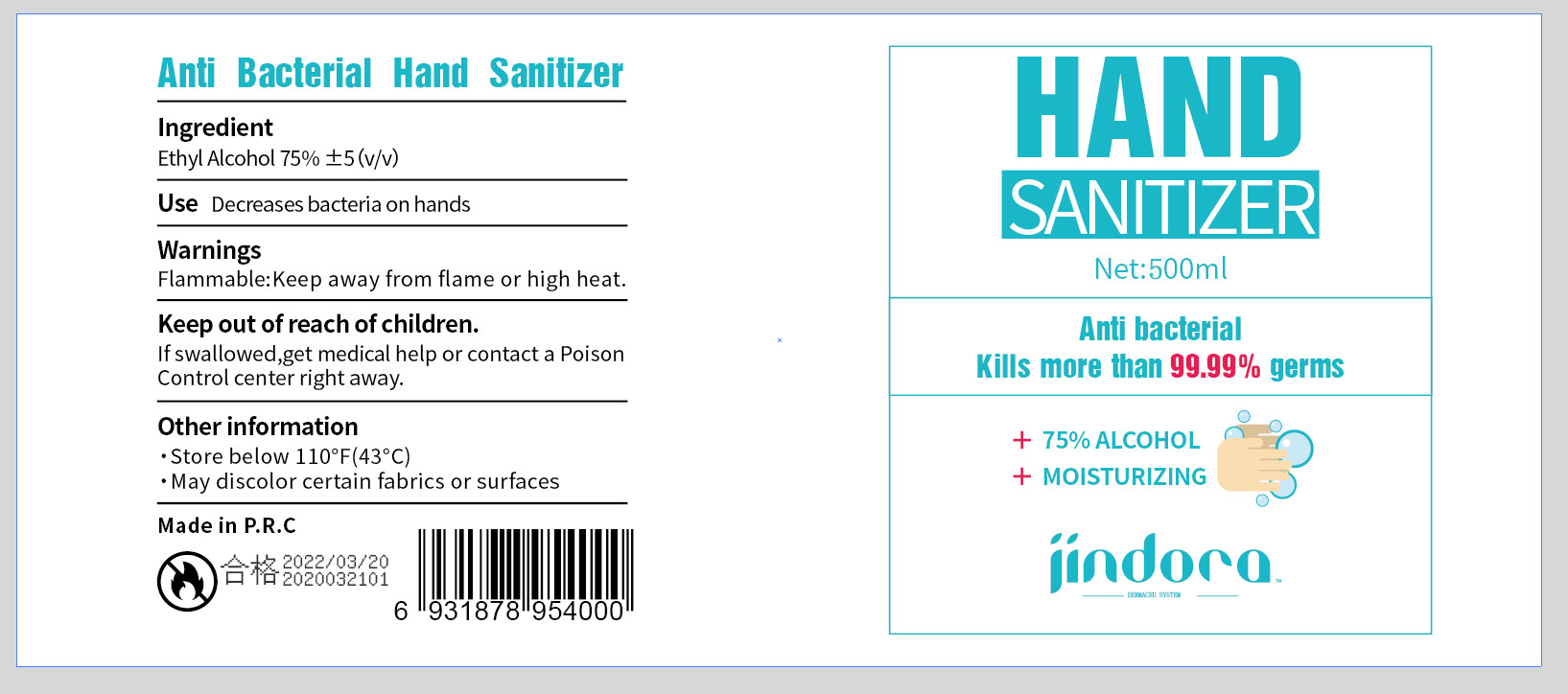 DRUG LABEL: not have
NDC: 75436-001 | Form: GEL
Manufacturer: Guangzhou Branson Biotechnology Co., Ltd
Category: otc | Type: HUMAN OTC DRUG LABEL
Date: 20200428

ACTIVE INGREDIENTS: ALCOHOL 75 mL/100 mL
INACTIVE INGREDIENTS: WATER

Anti Bacterial Hand Sanitizer

Active Ingredient

Ethyl Alcohol 75%±5(v/v)

Use

Decreases bacteria on hands

Warnings

Flammable:Keep away from flame or high heat.

Keep out of reach of children

If swallowed, get medical help or contact a Poison Control center right away.

Other information

Store below 110°F(43°C)

May discolor certain fabrics or surfaces